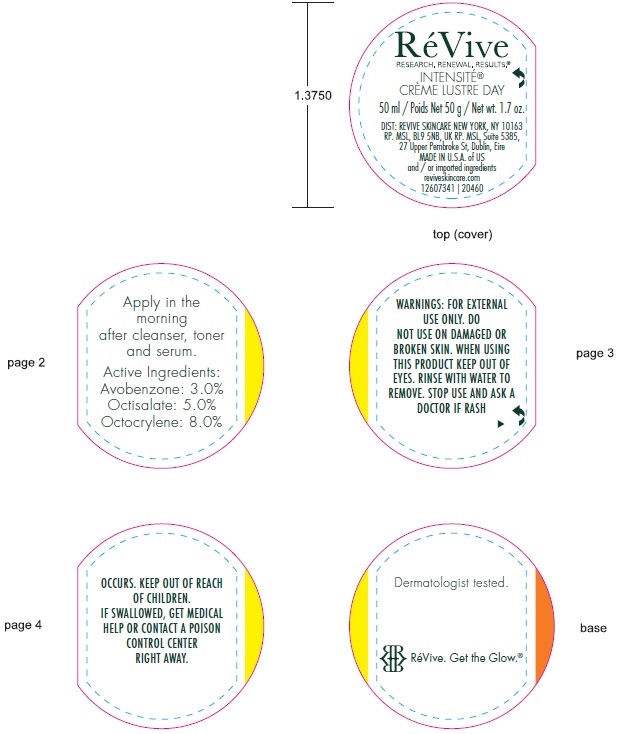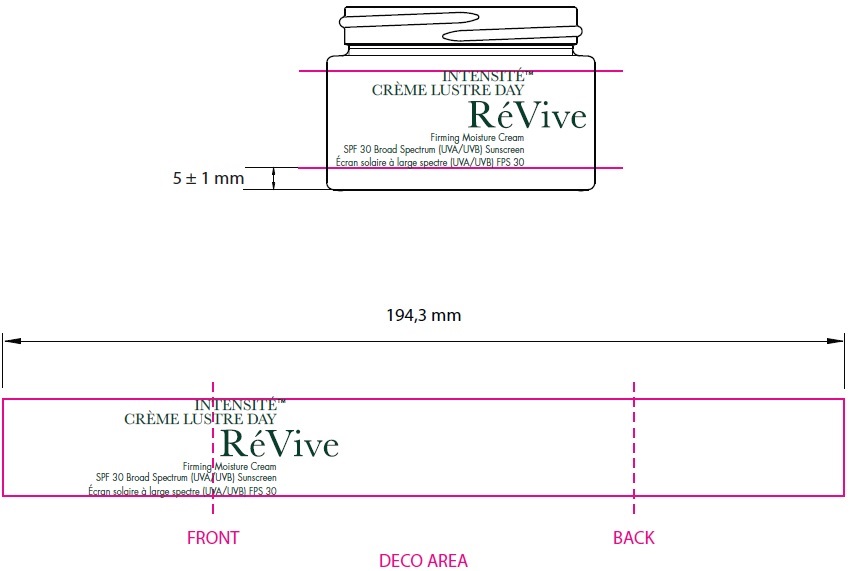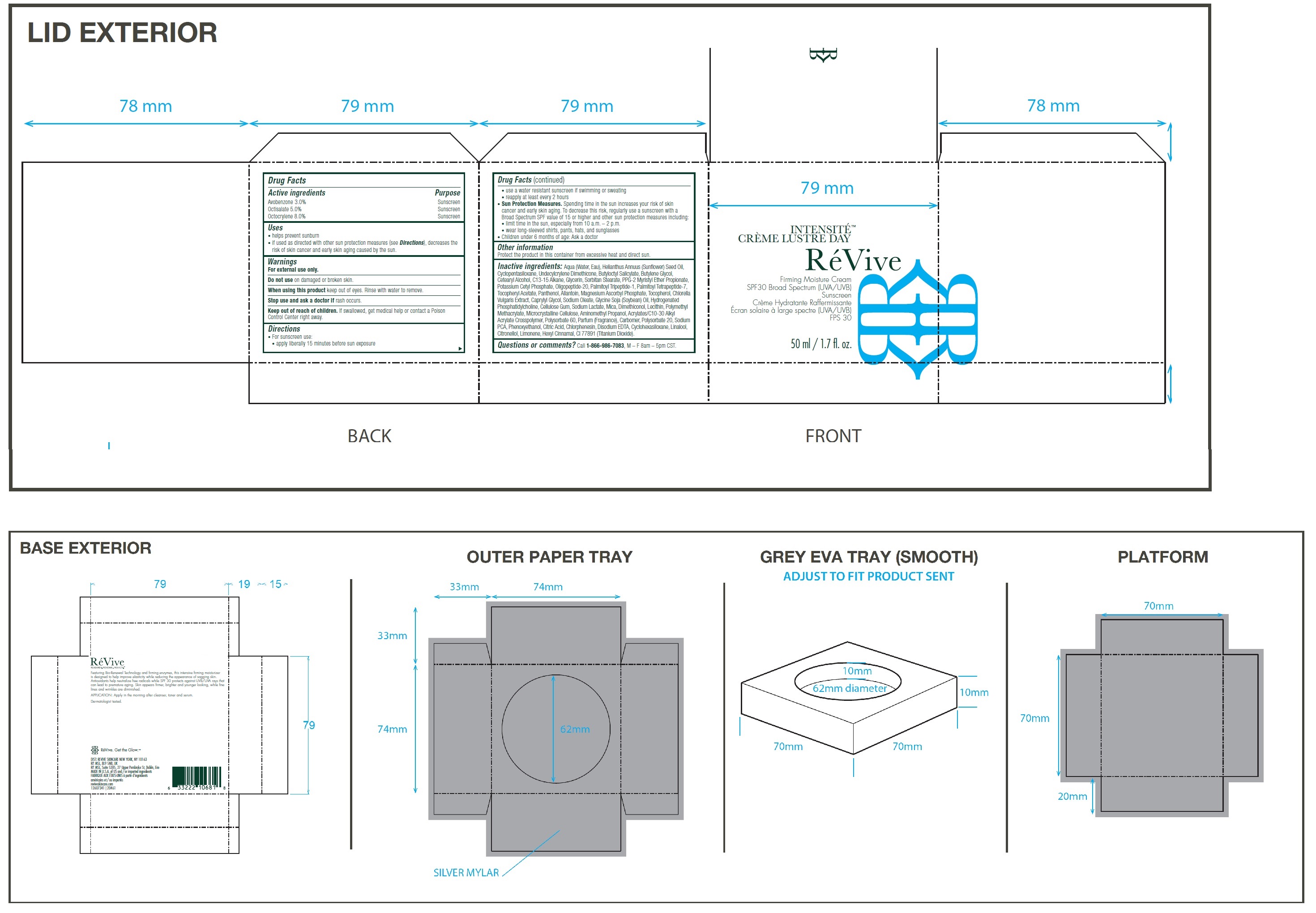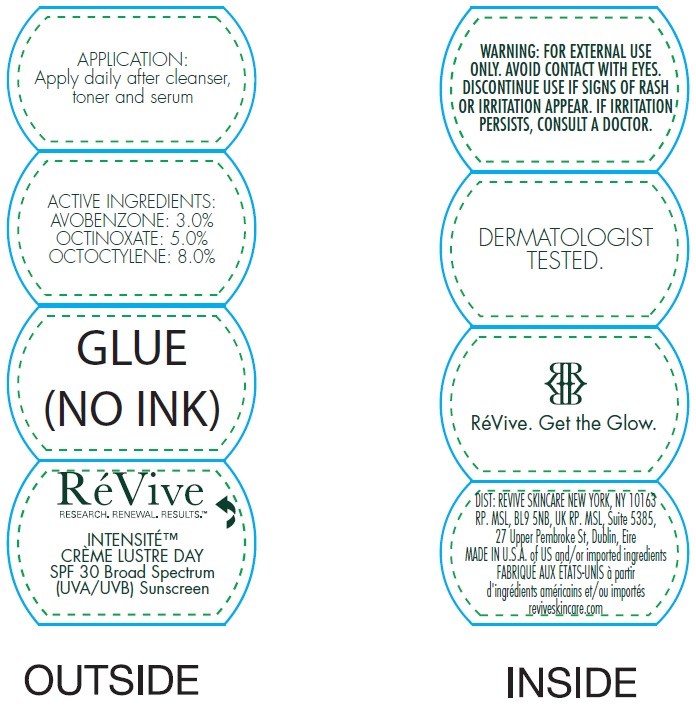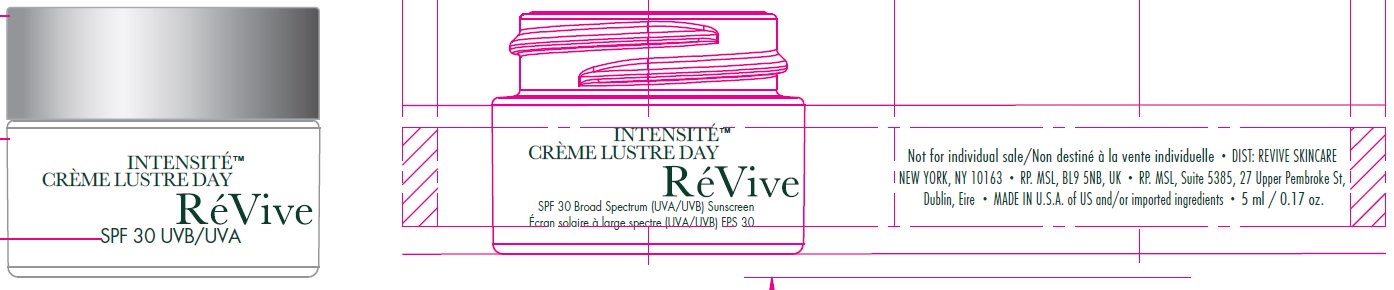 DRUG LABEL: Intensite Creme Lustre Day SPF 30 US
NDC: 82691-142 | Form: CREAM
Manufacturer: RV Skincare LLC
Category: otc | Type: HUMAN OTC DRUG LABEL
Date: 20231106

ACTIVE INGREDIENTS: AVOBENZONE 30 mg/1 mL; OCTISALATE 50 mg/1 mL; OCTOCRYLENE 80 mg/1 mL
INACTIVE INGREDIENTS: WATER; SUNFLOWER OIL; CYCLOMETHICONE 5; UNDECYLCRYLENE DIMETHICONE (10000 MW); BUTYLOCTYL SALICYLATE; BUTYLENE GLYCOL; CETOSTEARYL ALCOHOL; C13-15 ALKANE; GLYCERIN; SORBITAN MONOSTEARATE; PPG-2 MYRISTYL ETHER PROPIONATE; POTASSIUM CETYL PHOSPHATE; PALMITOYL TRIPEPTIDE-1; PALMITOYL TETRAPEPTIDE-7; .ALPHA.-TOCOPHEROL ACETATE; PANTHENOL; ALLANTOIN; MAGNESIUM ASCORBYL PHOSPHATE; TOCOPHEROL; CHLORELLA VULGARIS; CAPRYLYL GLYCOL; SODIUM OLEATE; SOYBEAN OIL; CARBOXYMETHYLCELLULOSE SODIUM, UNSPECIFIED; SODIUM LACTATE; MICA; MICROCRYSTALLINE CELLULOSE; AMINOMETHYLPROPANOL; POLYSORBATE 60; CARBOMER HOMOPOLYMER, UNSPECIFIED TYPE; POLYSORBATE 20; SODIUM PYRROLIDONE CARBOXYLATE; PHENOXYETHANOL; CITRIC ACID MONOHYDRATE; CHLORPHENESIN; EDETATE DISODIUM ANHYDROUS; CYCLOMETHICONE 6; LINALOOL, (+/-)-; .BETA.-CITRONELLOL, (R)-; LIMONENE, (+)-; .ALPHA.-HEXYLCINNAMALDEHYDE; TITANIUM DIOXIDE

Intensite Creme Lustre Day SPF 30 US

Active ingredients

Avobenzone 3.0%

Octisalate 5.0%

Octocrylene 8.0%

Purpose

Sunscreen

Uses

• helps prevent sunburn

• if used as directed with other sun protection measures (see Directions), decreases the risk of skin cancer and early skin aging caused by the sun.

Warnings

For external use only.

Do not use

on damaged or broken skin.

When using this product

keep out of eyes. Rinse with water to remove.

Stop use and ask a doctor if

rash occurs.

Keep out of reach of children.

If swallowed, get medical help or contact a Poison Control Center right away.

Directions

• For sunscreen use: • apply liberally 15 minutes before sun exposure • use a water resistant sunscreen if swimming or sweating • reapply at least every 2 hours • Spending time in the sun increases your risk of skin cancer and early skin aging. To decrease this risk, regularly use a sunscreen with a Broad Spectrum SPF value of 15 or higher and other sun protection measures including: • limit time in the sun, especially from 10 a.m. – 2 p.m. • wear long-sleeved shirts, pants, hats, and sunglasses • Children under 6 months of age: Ask a doctor
Sun Protection Measures.

Other information

Protect the product in this container from excessive heat and direct sun.

Inactive ingredients:

Aqua (Water, Eau), Helianthus Annuus (Sunflower) Seed Oil, Cyclopentasiloxane, Undecylcrylene Dimethicone, Butyloctyl Salicylate, Butylene Glycol, Cetearyl Alcohol, C13-15 Alkane, Glycerin, Sorbitan Stearate, PPG-2 Myristyl Ether Propionate, Potassium Cetyl Phosphate, Oligopeptide-20, Palmitoyl Tripeptide-1, Palmitoyl Tetrapeptide-7, Tocopheryl Acetate, Panthenol, Allantoin, Magnesium Ascorbyl Phosphate, Tocopherol, Chlorella Vulgaris Extract, Caprylyl Glycol, Sodium Oleate, Glycine Soja (Soybean) Oil, Hydrogenated Phosphatidylcholine, Cellulose Gum, Sodium Lactate, Mica, Dimethiconol, Lecithin, Polymethyl Methacrylate, Microcrystalline Cellulose, Aminomethyl Propanol, Acrylates/C10-30 Alkyl Acrylate Crosspolymer, Polysorbate 60, Parfum (Fragrance), Carbomer, Polysorbate 20, Sodium PCA, Phenoxyethanol, Citric Acid, Chlorphenesin, Disodium EDTA, Cyclohexasiloxane, Linalool, Citronellol, Limonene, Hexyl Cinnamal, CI 77891 (Titanium Dioxide).

Questions or comments?

Call , M – F 8am – 5pm CST. 1-866-986-7083